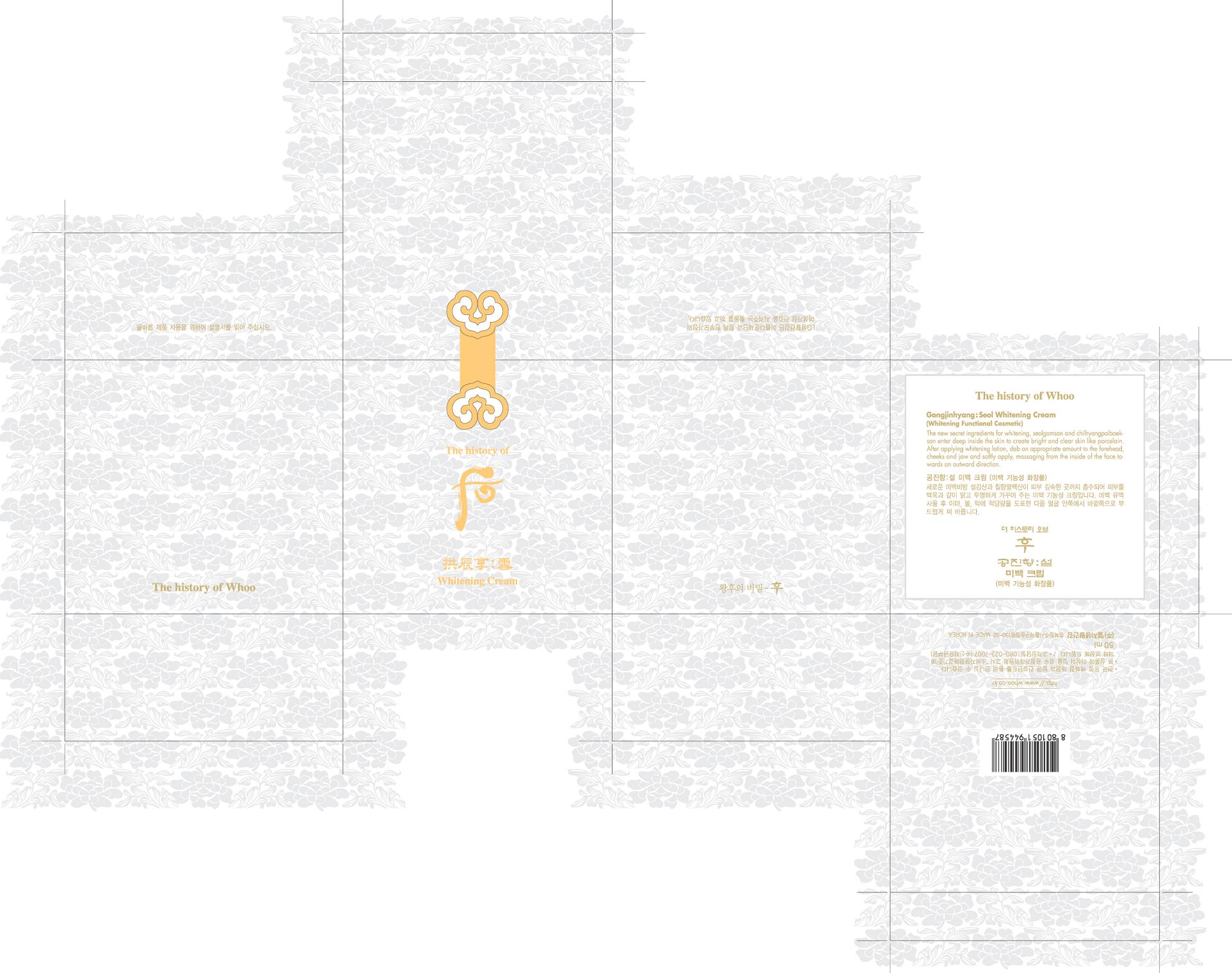 DRUG LABEL: GONGJINHYANG  SEOL WHITENING
NDC: 53208-504 | Form: CREAM
Manufacturer: LG Household and Healthcare, Inc.
Category: otc | Type: HUMAN OTC DRUG LABEL
Date: 20110315

ACTIVE INGREDIENTS: ATRACTYLODES JAPONICA ROOT OIL 0.05 mL/100 mL
INACTIVE INGREDIENTS: WATER; GLYCERIN; ALCOHOL; CYCLOMETHICONE 5; DIPROPYLENE GLYCOL; MEDIUM-CHAIN TRIGLYCERIDES; 1,2-HEXANEDIOL; TEA LEAF; POLYETHYLENE GLYCOL 6000; TROMETHAMINE; EDETATE TRISODIUM

Drug Fact

ACTIVE INGREDIENT

ATRACTYLODES JAPONICA ROOT OIL 0.05%

WARNINGS

For external use only.

Keep out of reach of children. Is swallowed, get medical help or contact a Poison Control Center right away.

WHEN USING

Keep out of eyes. Rinse with water to remove.

Stop use if a rash or irritation develops and lasts.

PURPOSE

Whitening functional cosmetic.

INDICATIONS AND USAGE

The last step in basic skin care, dispense pea-sized amount and apply the cream.

INACTIVE INGREDIENT

WATER, DIPROPYLENE GLYCOL, GLYCERIN, CYCLOMETHICONE 5, ALCOHOL, PANTHENOL, MEDIUM-CHAIN TRIGLYCERIDES, 1,2-HEXANEDIOL, TEA LEAF, POLYETHYLENE GLYCOL 6000, TROMETHAMINE, EDETATE TRISODIUM.

DOSAGE AND ADMINISTRATION

Use as the last step of skin care.

PACKAGE LABEL

The History of Whoo Gongjinhyang: Seol Whitening Cream